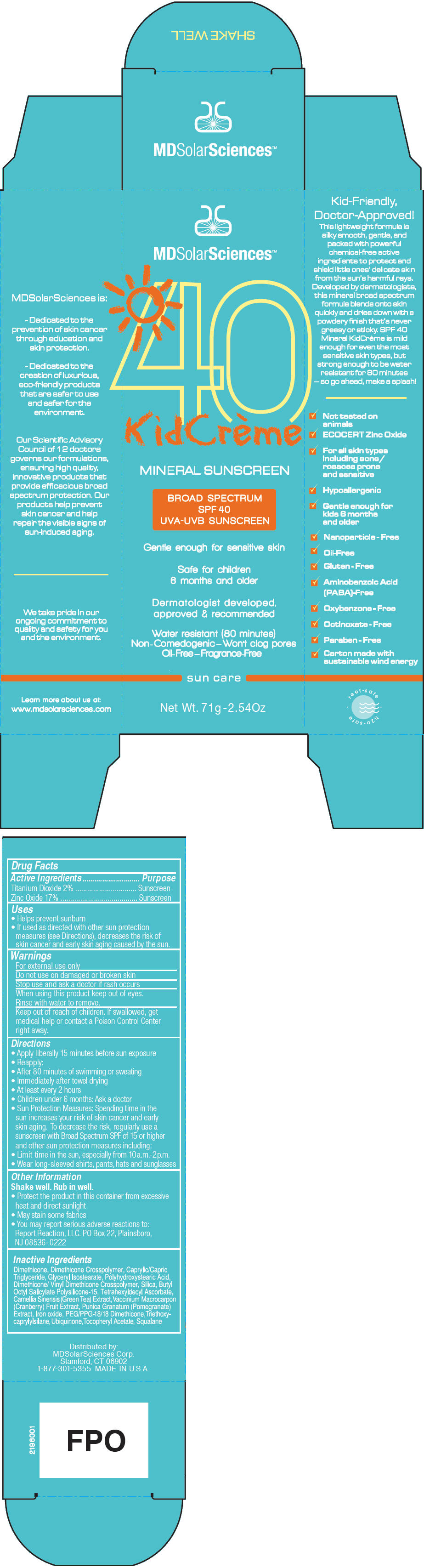 DRUG LABEL: KidCreme 
NDC: 49358-559 | Form: CREAM
Manufacturer: MDSolarSciences
Category: otc | Type: HUMAN OTC DRUG LABEL
Date: 20181025

ACTIVE INGREDIENTS: Titanium Dioxide 2.7 g/35 g; Zinc Oxide 1.3 g/35 g
INACTIVE INGREDIENTS: Dimethicone; DIMETHICONE/DIENE DIMETHICONE CROSSPOLYMER; MEDIUM-CHAIN TRIGLYCERIDES; GLYCERYL ISOSTEARATE; POLYHYDROXYSTEARIC ACID (2300 MW); DIMETHICONE/VINYL DIMETHICONE CROSSPOLYMER (SOFT PARTICLE); SILICON DIOXIDE; BUTYLOCTYL SALICYLATE; POLYSILICONE-15; TETRAHEXYLDECYL ASCORBATE; GREEN TEA LEAF; CRANBERRY; POMEGRANATE JUICE; FERRIC OXIDE RED; PEG/PPG-18/18 DIMETHICONE; TRIETHOXYCAPRYLYLSILANE; UBIDECARENONE; .ALPHA.-TOCOPHEROL ACETATE; SQUALANE

KidCrème
Mineral Broad Spectrum SPF 40 Sunscreen UVA-UVB Suncreen

Drug Facts

ACTIVE INGREDIENT

Active Ingredients | Purpose
Titanium Dioxide 2% | Sunscreen
Zinc Oxide 17% | Sunscreen

Uses

- Helps prevent sunburn
- If used as directed with other sun protection measures (see Directions), decreases the risk of skin cancer and early skin aging caused by the sun.

Warnings

For external use only

Do not use on damaged or broken skin

Stop use and ask a doctor if rash occurs

When using this product keep out of eyes. Rinse with water to remove.

Keep out of reach of children. If swallowed, get medical help or contact a Poison Control Center right away.

Directions

- Apply liberally 15 minutes before sun exposure
- Reapply:
  - After 80 minutes of swimming or sweating
  - Immediately after towel drying
  - At least every 2 hours
- Children under 6 months: Ask a doctor
- Sun Protection Measures: Spending time in the sun increases your risk of skin cancer and early skin aging. To decrease the risk, regularly use a sunscreen with Broad Spectrum SPF of 15 or higher and other sun protection measures including:
  - Limit time in the sun, especially from 10a.m.-2p.m.
  - Wear long-sleeved shirts, pants, hats and sunglasses

Other Information

Shake well. Rub in well.

- Protect the product in this container from excessive heat and direct sunlight
- May stain some fabrics
- You may report serious adverse reactions to: Report Reaction, LLC. PO Box 22, Plainsboro, NJ 08536-0222

Inactive Ingredients

Dimethicone, Dimethicone Crosspolymer, Caprylic/Capric Triglyceride, Glyceryl Isostearate, Polyhydroxystearic Acid, Dimethicone/ Vinyl Dimethicone Crosspolymer, Silica, Butyl Octyl Salicylate Polysilicone-15, Tetrahexyldecyl Ascorbate, Camellia Sinensis (Green Tea) Extract, Vaccinium Macrocarpon (Cranberry) Fruit Extract, Punica Granatum (Pomegranate) Extract, Iron oxide, PEG/PPG-18/18 Dimethicone, Triethoxy-caprylylsilane, Ubiquinone, Tocopheryl Acetate, Squalane

Distributed by:
MDSolarSciences Corp.
Stamford, CT 06902

PRINCIPAL DISPLAY PANEL - 71 g Tube Carton

MDSolarSciences™

40
KidCrème

MINERAL SUNSCREEN

BROAD SPECTRUM
SPF 40
UVA-UVB SUNSCREEN

Gentle enough for sensitive skin

Safe for children
6 months and older

Dermatologist developed,
approved & recommended

Water resistant (80 minutes)
Non-Comedogenic–Won't clog pores
Oil-Free–Fragrance-Free

sun care

Net Wt. 71g -2.54Oz